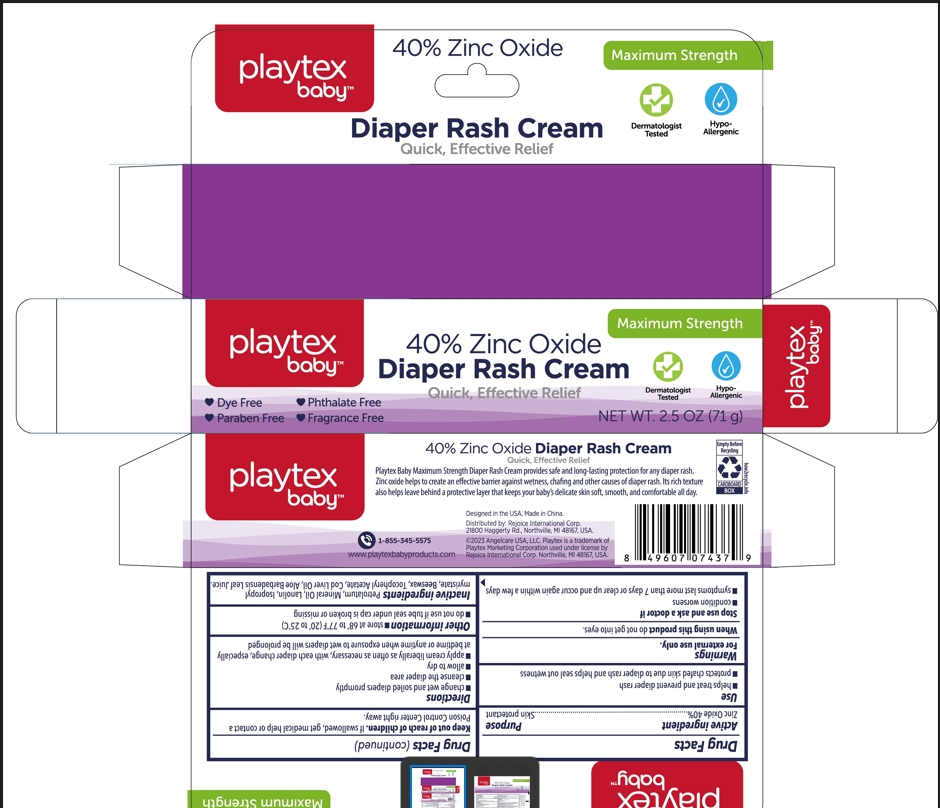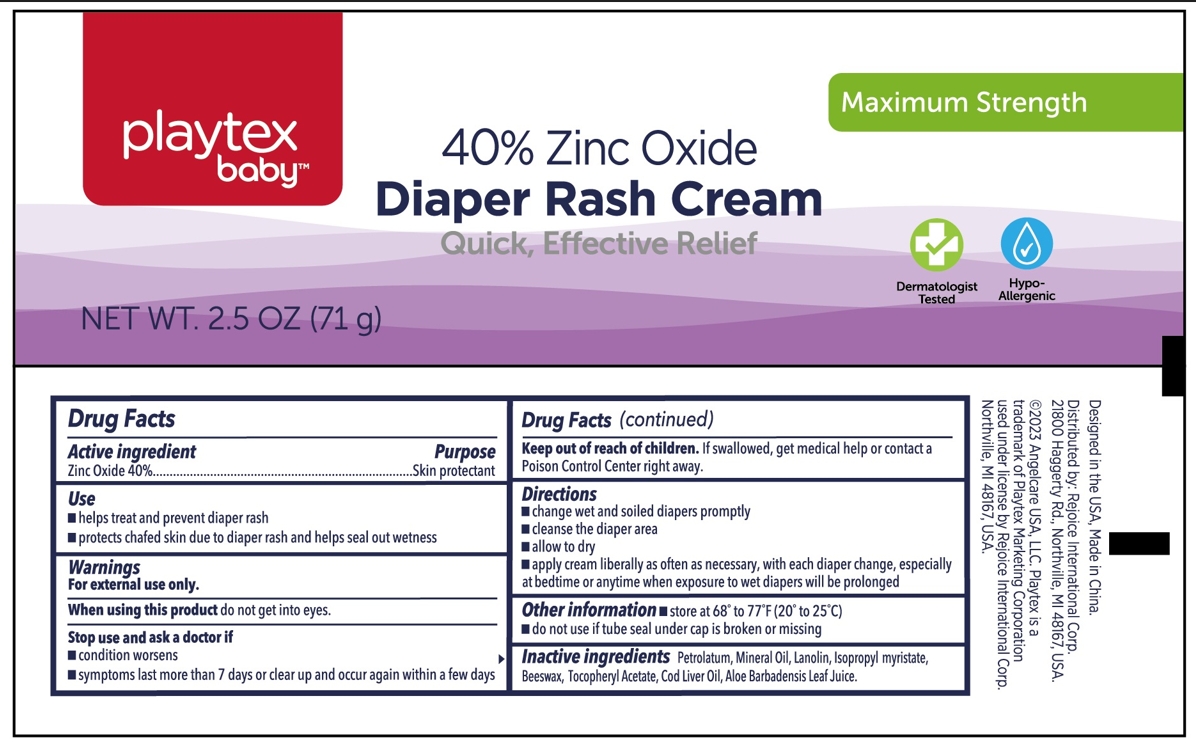 DRUG LABEL: Diaper Rash Cream 2.5oz
NDC: 57337-151 | Form: CREAM
Manufacturer: Rejoice International Corp.
Category: otc | Type: HUMAN OTC DRUG LABEL
Date: 20231204

ACTIVE INGREDIENTS: ZINC OXIDE 0.4 g/1 g
INACTIVE INGREDIENTS: LANOLIN; MINERAL OIL; ISOPROPYL MYRISTATE; COD LIVER OIL; ALOE VERA LEAF; .ALPHA.-TOCOPHEROL ACETATE; PETROLATUM; YELLOW WAX

Active ingredient

Zinc Oxide 40%

Purpose

Skin protectant

Use

- helps treat and prevent diaper rash
- protects chafed skin due to diaper rash and helps seal out wetness

Warnings

For external use only

Stop use and ask a doctor if

- condition worsen
- symptoms last more than 7 days or clear up and occur again within a few days

When using this product do not get into eyes.

Keep out of reach of children

If swallowed, get medical help or contact a Poison Control Center right away.

Directions

- change wet and soilded diapers promtly
- cleanse the diaper area
- allow to dry
- apply cream liberally as often as necessary, with each diaper change, especially at bedtime or anytime when exposure to wet diapers will be prolonged.

Other information

- store at 68º-77ºF(20º to 25ºC)
- do not use if tube seal under cap is broken or missing

Inactive ingredients

Petrolatum

Mineral Oil

Lanolin

Isopropyl Myristate

Beeswax

Tocopheryl Acetate

Cod Liver Oil

Aloe Barbadensis Leaf Juice